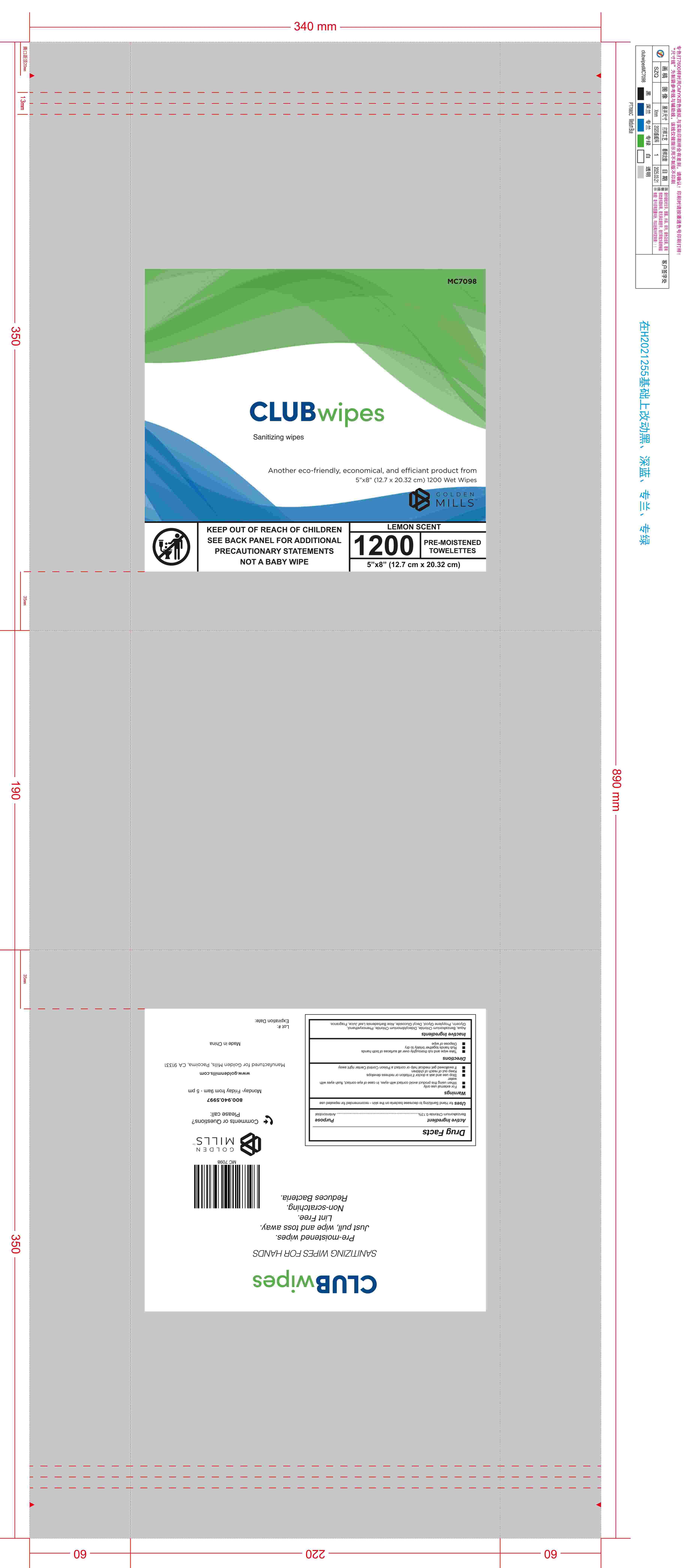 DRUG LABEL: Club Wipes Sanitizing Wipes,Lemon Scent,1200ct
NDC: 85989-001 | Form: PATCH
Manufacturer: Hangzhou Yida Technology Co., Ltd.
Category: otc | Type: HUMAN OTC DRUG LABEL
Date: 20251103

ACTIVE INGREDIENTS: BENZALKONIUM CHLORIDE 1.3 mg/1 g
INACTIVE INGREDIENTS: GLYCERIN; ALOE VERA LEAF; WATER; DECYL GLUCOSIDE

ACTIVE INGREDIENT

Benzalkonium Chloride 0.13% Purpose - Antimicrobial

PURPOSE

for Hand Sanitizing to decrease on the skin - recommended for repeated use

KEEP OUT OF REACH OF CHILDREN

If swallowed get medical help or contact a Poison Control Center right away

WARNINGS

For external use only

When using this product

avoid contact with eyes. In case of eye contact, flush eyes with water

Stop use and ask a doctor

if irritation or redness develops

DOSAGE AND ADMINISTRATION

Take wipe and rub thoroughly over all surfaces or both hands

INDICATIONS AND USAGE

Rub hands together briskly to dry
Dispose of wipe

INACTIVE INGREDIENT

Purified Water, Glycerin, Aloe Barbadensis Leaf Juice, Decyl Glucoside